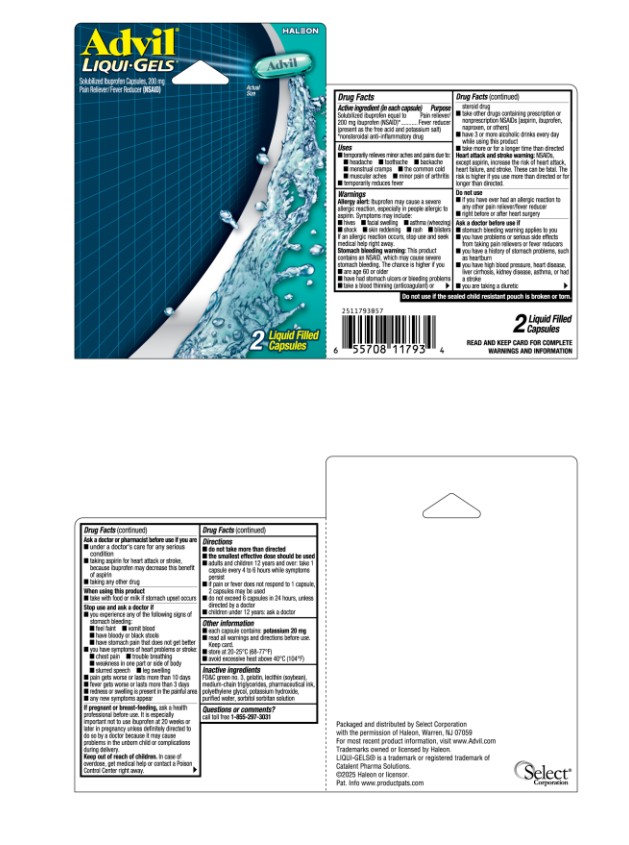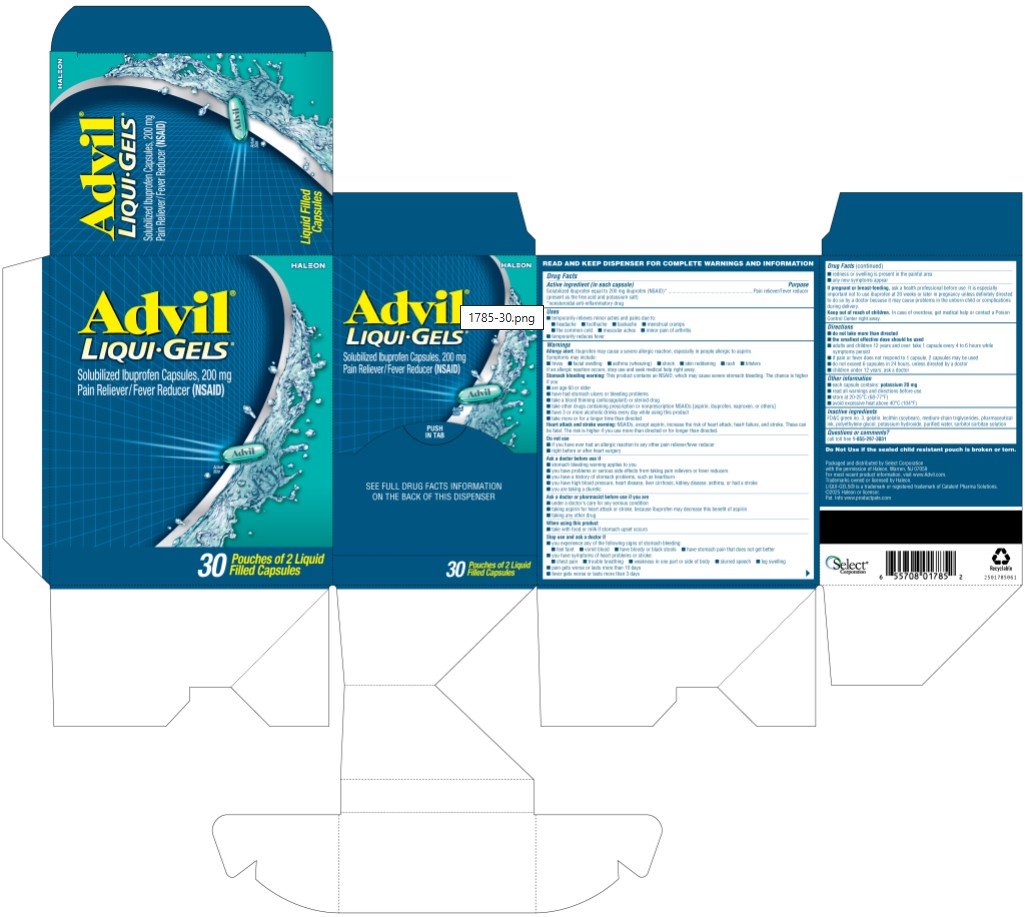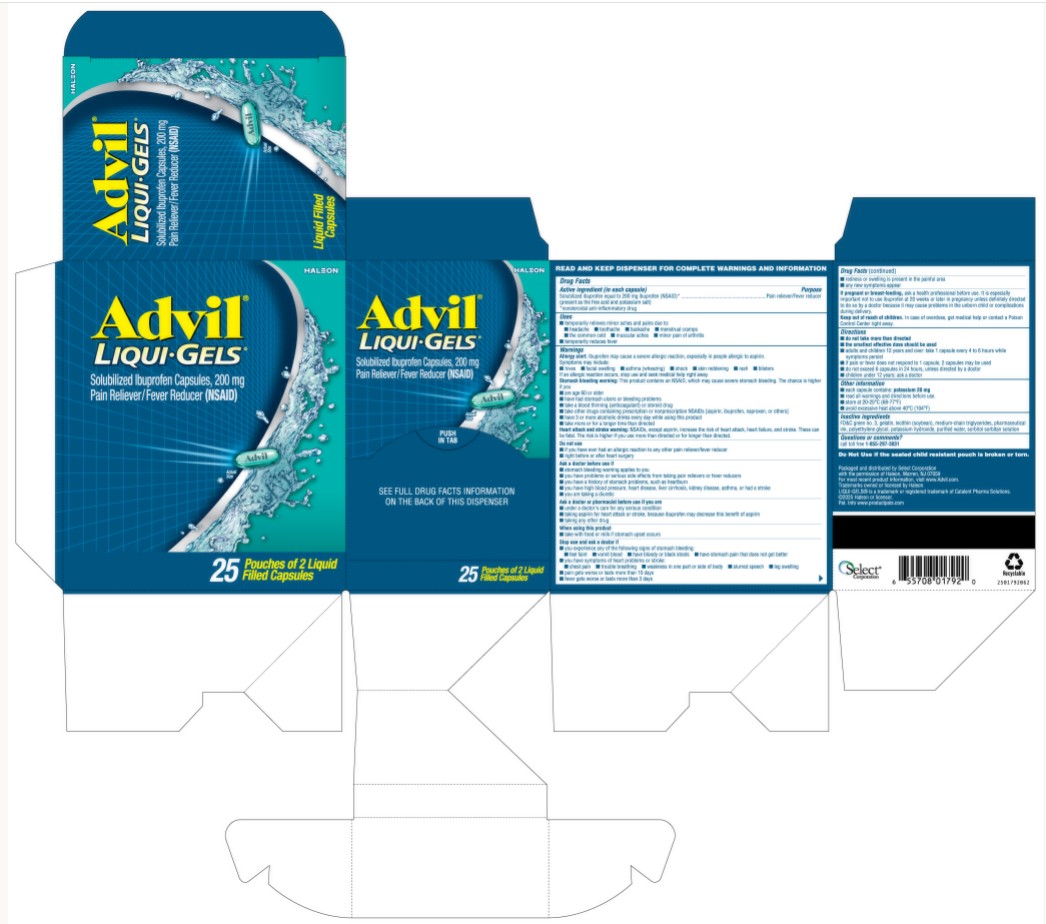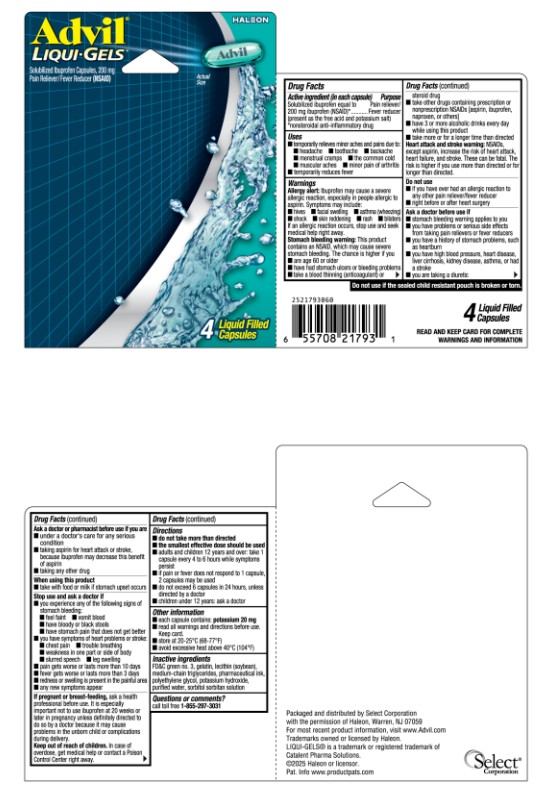 DRUG LABEL: Advil Liquigel
NDC: 85237-1785 | Form: CAPSULE, LIQUID FILLED
Manufacturer: Select Consumer Group
Category: otc | Type: HUMAN OTC DRUG LABEL
Date: 20251228

ACTIVE INGREDIENTS: IBUPROFEN 200 mg/1 1
INACTIVE INGREDIENTS: FD&C GREEN NO. 3; GELATIN, UNSPECIFIED; SOYBEAN LECITHIN; MEDIUM-CHAIN TRIGLYCERIDES; POLYETHYLENE GLYCOL, UNSPECIFIED; POTASSIUM HYDROXIDE; WATER; SORBITAN; SORBITOL

Drug Facts

Active ingredient (in each capsule)

Solubilized ibuprofen equal to 200 mg ibuprofen (NSAID)*

(present as the free acid and potassium salt)

*nonsteroidal anti-inflammatory drug

Purpose

Pain reliever/Fever reducer

Uses

- temporarily relieves minor aches and pains due to:
  - headache
  - toothache
  - backache
  - menstrual cramps
  - the common cold
  - muscular aches
  - minor pain of arthritis
- temporarily reduces fever

Warnings

Allergy alert:

Ibuprofen may cause a severe allergic reaction, especially in people allergic to aspirin. Symptoms may include:

- hives
- facial swelling
- asthma (wheezing)
- shock
- skin reddening
- rash
- blisters

If an allergic reaction occurs, stop use and seek medical help right away.

Stomach bleeding warning:

This product contains an NSAID, which may cause severe stomach bleeding. The chance is higher if you

- are age 60 or older
- have had stomach ulcers or bleeding problems
- take a blood thinning (anticoagulant) or steroid drug
- take other drugs containing prescription or nonprescription NSAIDs [aspirin, ibuprofen, naproxen, or others]
- have 3 or more alcoholic drinks every day while using this product
- take more or for a longer time than directed

Heart attack and stroke warning:

NSAIDs, except aspirin, increase the risk of heart attack, heart failure, and stroke. These can be fatal. The risk is higher if you use more than directed or for longer than directed.

Do not use

- if you have ever had an allergic reaction to any other pain reliever/fever reducer
- right before or after heart surgery

Ask a doctor before use if

- stomach bleeding warning applies to you
- you have problems or serious side effects from taking pain relievers or fever reducers
- you have a history of stomach problems, such as heartburn
- you have high blood pressure, heart disease, liver cirrhosis, kidney disease, asthma, or had a stroke
- you are taking a diuretic

Ask a doctor or pharmacist before use if you are

- under a doctor's care for any serious condition
- taking aspirin for heart attack or stroke, because ibuprofen may decrease this benefit of aspirin
- taking any other drug

When using this product

- take with food or milk if stomach upset occurs

Stop use and ask a doctor if

- you experience any of the following signs of stomach bleeding:
  - feel faint
  - vomit blood
  - have bloody or black stools
  - have stomach pain that does not get better
- you have symptoms of heart problems or stroke:
  - chest pain
  - trouble breathing
  - weakness in one part or side of body
  - slurred speech
  - leg swelling
- pain gets worse or lasts more than 10 days
- fever gets worse or lasts more than 3 days
- redness or swelling is present in the painful area
- any new symptoms appear

If pregnant or breast-feeding,

ask a health professional before use. It is especially important not to use ibuprofen at 20 weeks or later in pregnancy unless definitely directed to do so by a doctor because it may cause problems in the unborn child or complications during delivery.

Keep out of reach of children.

In case of overdose, get medical help or contact a Poison Control Center right away.

Directions

- do not take more than directed
- the smallest effective dose should be used
- adults and children 12 years and over: take 1 capsule every 4 to 6 hours while symptoms persist
- if pain or fever does not respond to 1 capsule, 2 capsules may be used
- do not exceed 6 capsules in 24 hours, unless directed by a doctor
- children under 12 years: ask a doctor

Other information

- each capsule contains: potassium 20 mg
- read all warnings and directions before use. Keep carton.
- store at 20-25°C (68-77°F)
- avoid excessive heat above 40°C (104°F)

Inactive ingredients

Advil Liqui-Gels

FD&C green no. 3, gelatin, lecithin (soybean), medium-chain triglycerides, pharmaceutical ink, polyethylene glycol, potassium hydroxide, purified water, sorbitol sorbitan solution

Advil Liqui-Gels Minis

FD&C green no. 3, gelatin, medium-chain triglycerides, pharmaceutical ink, polyethylene glycol, potassium hydroxide, purified water, sorbitol sorbitan solution

Questions or comments?

call toll free 1-800-88-ADVIL